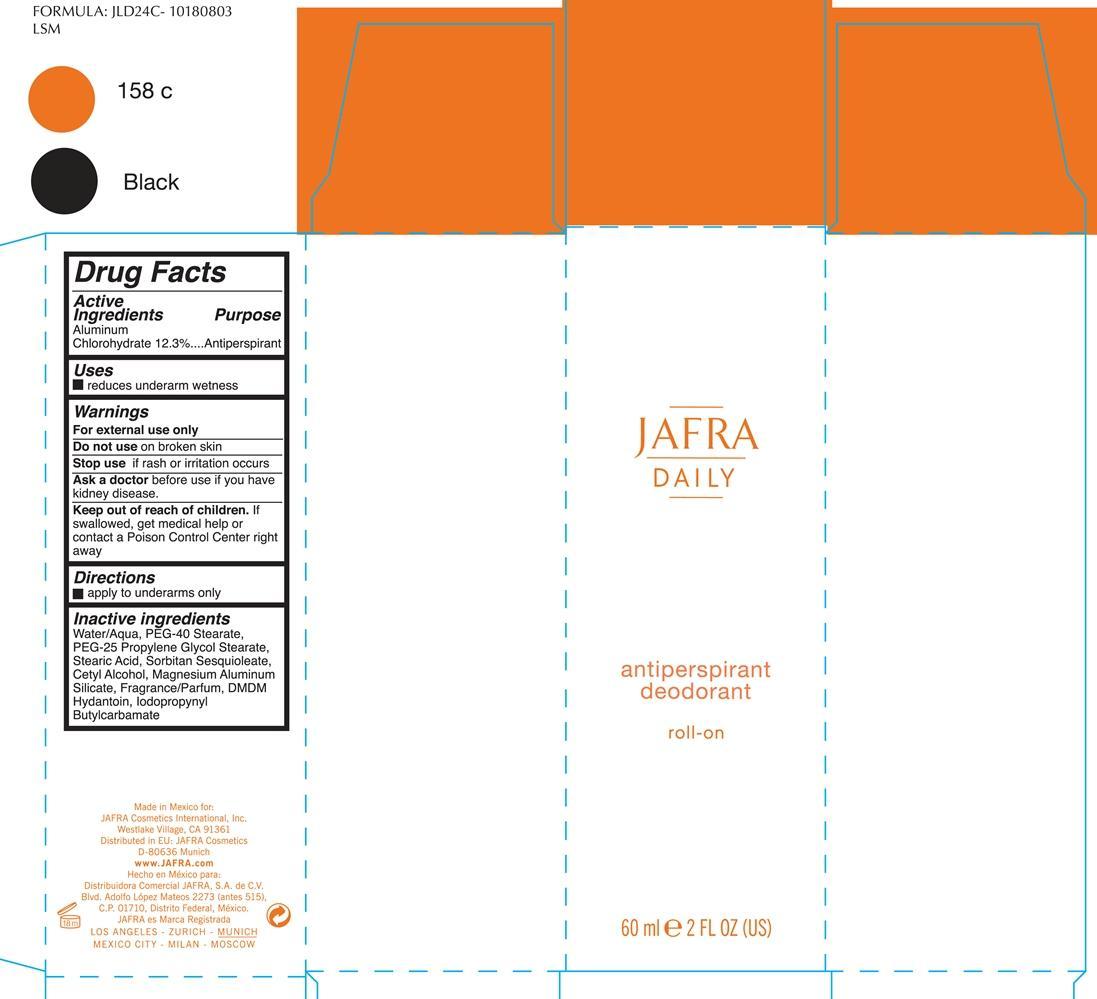 DRUG LABEL: Antiperspirant Deodorant Roll-on

NDC: 68828-198 | Form: LIQUID
Manufacturer: Jafra cosmetics International
Category: otc | Type: HUMAN OTC DRUG LABEL
Date: 20200622

ACTIVE INGREDIENTS: ALUMINUM CHLOROHYDRATE 12.3 g/100 mL
INACTIVE INGREDIENTS: WATER; PEG-40 STEARATE; PEG-25 PROPYLENE GLYCOL STEARATE; STEARIC ACID; SORBITAN SESQUIOLEATE; CETOSTEARYL ALCOHOL; MAGNESIUM ALUMINUM SILICATE; DMDM HYDANTOIN; IODOPROPYNYL BUTYLCARBAMATE

Jafra Daily antiperspirant deodorant roll on

Active Ingredients Purpose

Aluminum Chlorohydrate 12.3% Antiperspirant

Uses

Reduces underarm wetness

Keep out of reach of children. If swallowed, get medical help or contact a Poison Control Center right away.

Stop use if rash or irritation occurs

Warnings

For external use only

Do not use on broken skin

Ask a doctor before use if you have kidney disease

DOSAGE AND ADMINISTRATION

apply to underarms only

INACTIVE INGREDIENT

Water/Aqua, PEG-40 Stearate, PEG-25 Propylene Glycol Stearate, Stearic Acid, Sorbitan Sesquioleate, Cetyl Alcohol, Magnesium Aluminum Silicate, Fragrance/parfum, DMDM hydantoin, Iodopropynyl Butylcarbamate

PACKAGE LABEL

Jafra Daily

antiperspirant

deodorant
roll-on

60 ml 2 Fl Oz (US)